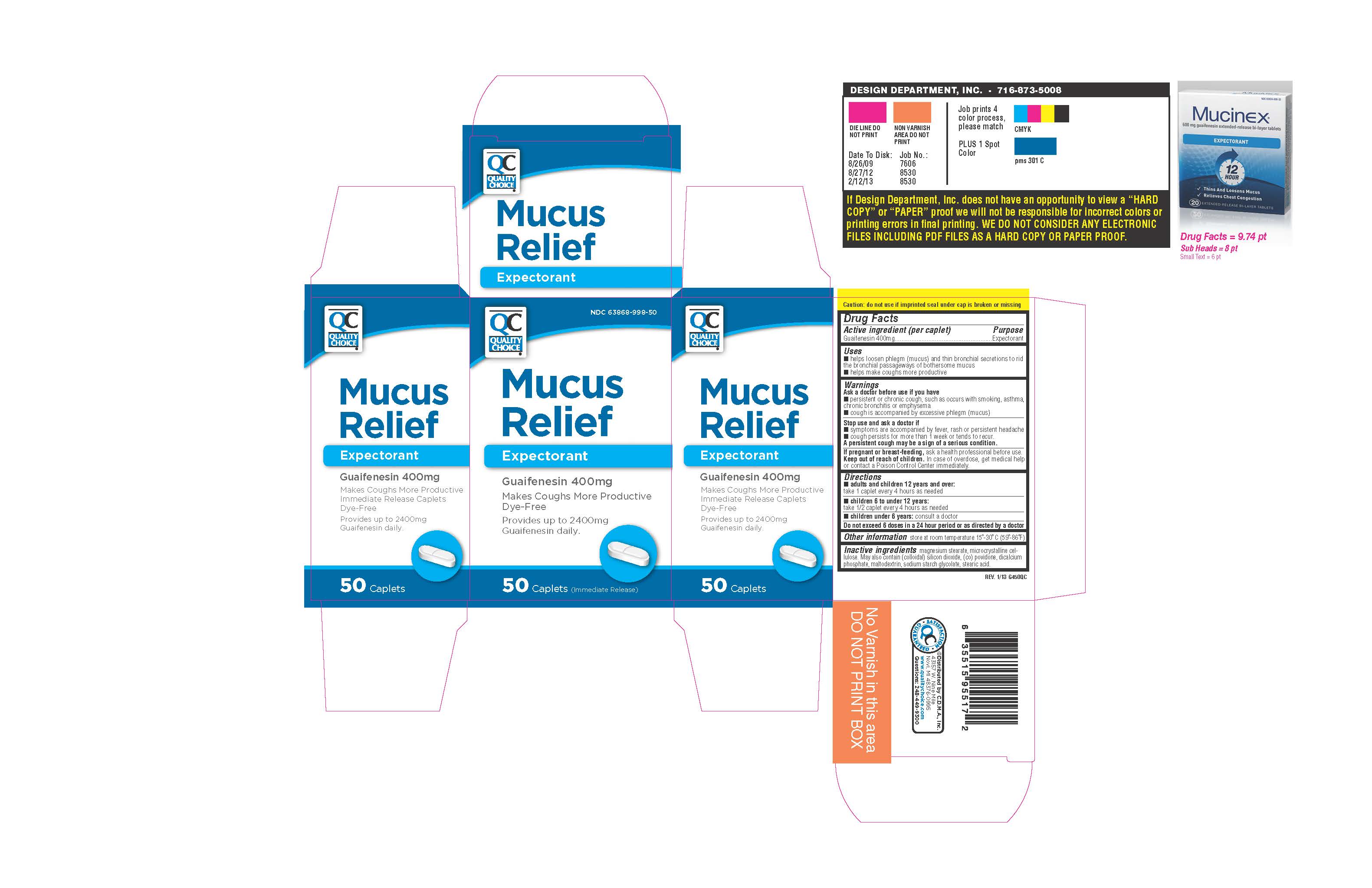 DRUG LABEL: Quality Choice Mucus Relief
NDC: 83324-194 | Form: TABLET
Manufacturer: Chain Drug Marketing Association
Category: otc | Type: HUMAN OTC DRUG LABEL
Date: 20251202

ACTIVE INGREDIENTS: Guaifenesin 400 mg/1 1
INACTIVE INGREDIENTS: MALTODEXTRIN; STEARIC ACID; SILICON DIOXIDE; COPOVIDONE; MAGNESIUM STEARATE

Drug Facts

Active ingredient (per tablet)

Guaifenesin 400mg

Purpose

Expectorant

Uses

- helps loosen phlegm (mucus) and thin bronchial secretions to rid the bronchial passageways of bothersome mucus
- helps make coughs more productive

Warnings

Ask doctor before use if you have

- persistent or chronic cough, such as occurs with smoking, asthma, bronchitis or emphysema
- cough is accompanied by excessive phlegm (mucus)

Stop use and ask doctor if

- Symptoms are accompanied by fever, rash or persistent headache
- cough persists for more than 1 week or tends to recur

A persistent cough may be a sign of a serious condition.

PREGNANCY OR BREAST FEEDING

If pregnant or breast-feeding, ask a health professional before use.

Keep out of reach of children.
In case of overdose, get medical help or contact a Poison Control
Center immediately.

Directions

- Adults and children 12 years of age and over: take 1 tablet every 4 hours as needed
- Children 6 to 10 under 12 years of age: take 1/2 tablet every 4 hours as needed
- Children under 6 years of age: consult a doctor

Do not exceed 6 doses in a 24 hour period or as directed by a doctor

Other Information

store at 15°-30°C (59°-86°F)

Inactive ingredients

magnesium stearate, microcrystalline cellulose. May also contain (colloidal) silicon dioxide, (co) povidone, dicalcium phosphate, maltodextrin, sodium starch glycolate, stearic acid.